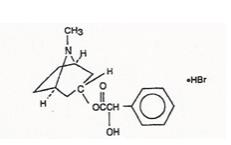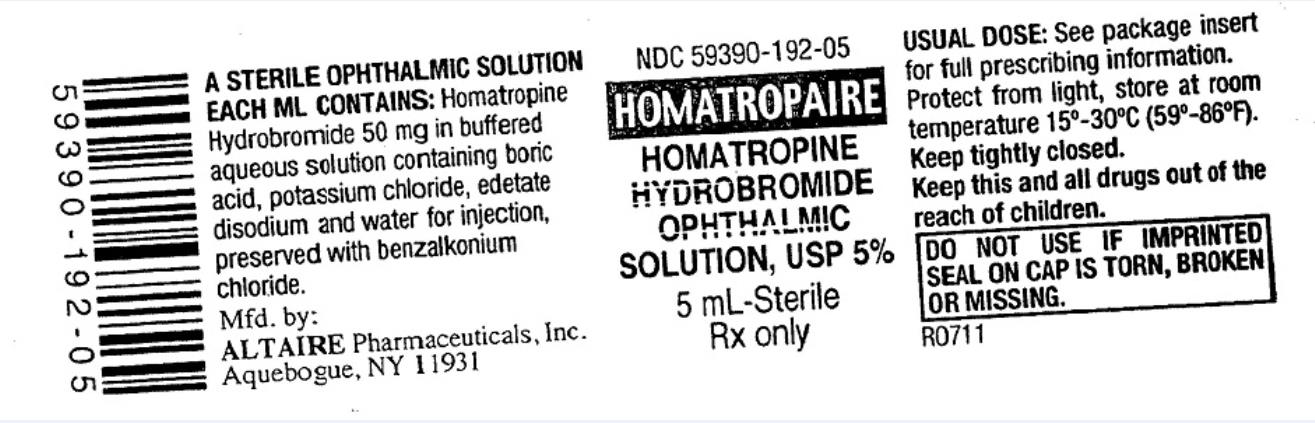 DRUG LABEL: HOMATROPINE HYDROBROMIDE OPHTHALMIC
NDC: 59390-192 | Form: SOLUTION
Manufacturer: Altaire Pharmaceuticals Inc.
Category: prescription | Type: HUMAN PRESCRIPTION DRUG LABEL
Date: 20221028

ACTIVE INGREDIENTS: HOMATROPINE HYDROBROMIDE 50 mg/1 mL
INACTIVE INGREDIENTS: BENZALKONIUM CHLORIDE; BORIC ACID; EDETATE DISODIUM; POTASSIUM CHLORIDE; WATER; SODIUM CARBONATE

Homatropine Hydrobromide Ophthalmic Solution, USP

HOMATROPINE HYDROBROMIDE
OPHTHALMIC SOLUTION, USP
Rx only

Established name:
Homatropine Hydrobromide

Chemical Name:
Benzeneacetic acid, ɑ-hydroxy-, 8-methyl-8-azabicyclo [3.2.1]-oct-3-yl ester, hydrobromide, endo-(±)-. The active ingredient is represented by the chemical structure:

Each mL contains: Active: Homatropine Hydrobromide 5.0%. Preservative: Benzalkonium Chloride 0.005%. Inactive: Boric Acid, Edetate Disodium, Potassium Chloride, Water for Injection. Boric Acid or Sodium Carbonate may be added to adjust the pH.

INDICATIONS AND USAGE:

A moderately long-acting mydriatic and cycloplegic for cycloplegic refraction and in the treatment of inflammatory conditions of the uveal tract. For pre and postoperative states when mydriasis is required. Use as an optical aid in some cases of axial lens opacities.

DOSAGE AND ADMINISTRATION:

For refraction, instill one or two drops topically in the eye(s). May be repeated in five or ten minutes if necessary. For uveitis, instill one or two drops topically up to every three to four hours. Individuals with heavily pigmented irides may require larger doses.

CONTRAINDICATIONS:

Contraindicated in persons with primary glaucoma or a tendency toward glaucoma, e.g. narrow anterior chamber angle, and in those persons showing hypersensitivity to any component of this preparation.

WARNING:

For topical use only – not for injection. Risk-benefit should be considered when the following medical problems exist: keratoconus (Homatropine may produce fixed dilated pupil); Down’s syndrome, children with brain damage and the elderly (increased susceptibility). In infants and small children, use with extreme caution. Excessive use in pediatric patients or certain individuals with a history of susceptibility to belladonna alkaloids may produce systemic symptoms of homatropine poisoning (see overdose section).

PRECAUTIONS:

General.

To avoid excessive systemic absorption, the lacrimal sac should be compressed by digital pressure for two to three minutes after installation. To avoid inducing angle closure glaucoma, an estimation of the depth of the angle of the anterior chamber should be made. Excessive topical use of this drug can potentially lead to a confusional state characterized by delirium, agitation, and rarely coma. This state is more apt to occur in the pediatric and geriatric age groups. The specific anti-dote for this systemic anticholinergic syndrome is injectable physostigmine salicylate.

Information to Patients.

Patient should be advised not to drive or engage in other hazardous activities while pupils are dilated. Patient may experience sensitivity to light and should protect eyes in bright illumination during dilation. Parents should be warned not to get this preparation in their child’s mouth and to wash their own hands and the child’s hands following administration. Do not touch dropper tip to any surface, as this may contaminate the solution.

ADVERSE REACTIONS:

Transient symptoms of stinging and burning may occur. Prolonged use may produce local irritation characterized by follicular conjunctivitis, vascular congestion, edema, exudates, and an eczematoid dermatitis. Thirst or dryness of mouth, eye irritation not present before therapy, or increased sensitivity of eyes to light may occur.

To report SUSPECTED ADVERSE REACTIONS, contact Altaire Pharmaceuticals, Inc. at (800)-258-2471.

Pregnancy.

Pregnancy Category C. Animal reproduction studies have not been conducted with homatropine hydrobromide. It is also not known whether homatropine hydrobromide can cause fetal harm when administered to a pregnant woman or can affect reproduction capacity. Homatropine Hydrobromide should be given to a pregnant woman only if clearly needed.

Nursing Mothers.

It is not known whether this drug is excreted in human milk. Because many drugs are excreted in human milk, caution should be exercised when homatropine hydrobromide is administered to a nursing woman

Pediatric Use:

Homatropine should not be used during the first three months of life due to a possible association between the cycloplegia produced and the development of amblyopia.

Safety and effectiveness in pediatric patients have not been established.

OVERDOSAGE:

When signs and symptoms of homatropine toxicity develop (see adverse reaction section), physostigmine should be administered parenterally (for dosage refer to Goodman & Gilman or other pharmacology reference). In infants and pediatric patients, the body surface must be kept moist.

DESCRIPTION:

Homatropine hydrobromide is an anticholinergic prepared as a sterile topical ophthalmic solution.

CLINICAL PHARMACOLOGY:

This anticholinergic preparation blocks the responses of the sphincter muscle of the iris and the accommodative muscle of the ciliary body to cholinergic stimulation, producing pupillary dilation (mydriasis) and paralysis of accommodation (cycloplegia).

Carcinogenesis, Mutagenesis, Impairment of Fertility:

There have been no long-term studies done using homatropine hydrobromide in animals to evaluate carcinogenic potential.

HOW SUPPLIED:

5mL size in a white plastic bottle
5mL - NDC 59390-192-05

Storage:

Store at 15° - 30°C (59°- 86°F).

Caution: Federal (USA) law prohibits dispensing without prescription.

Mfd. by: Altaire Pharmaceuticals, Inc
Aquebogue, NY 11931

R05/13
F# 16545

PACKAGE LABEL

PRINCIPAL DISPLAY PANEL

NDC 59390-192-05
Homatropaire
Homatropine Hydrobromide
Ophthalmic Solution, USP 5%
5 mL- Sterile
Rx Only